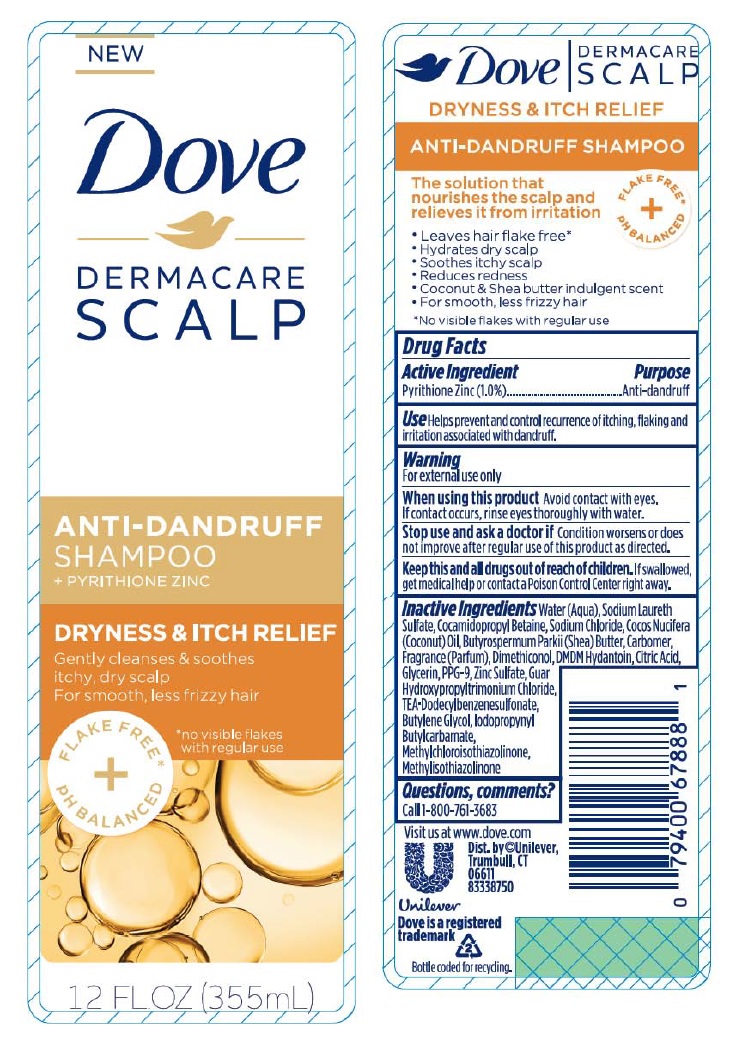 DRUG LABEL: Dove

NDC: 64942-1487 | Form: SHAMPOO
Manufacturer: Conopco, Inc. d/b/a/ Unilever
Category: otc | Type: HUMAN OTC DRUG LABEL
Date: 20210310

ACTIVE INGREDIENTS: PYRITHIONE ZINC 1 g/100 mL
INACTIVE INGREDIENTS: WATER; SODIUM LAURETH-3 SULFATE; COCAMIDOPROPYL BETAINE; SODIUM CHLORIDE; COCONUT OIL; SHEA BUTTER; CARBOMER HOMOPOLYMER TYPE C (ALLYL PENTAERYTHRITOL CROSSLINKED); DIMETHICONOL (40 CST); DMDM HYDANTOIN; CITRIC ACID MONOHYDRATE; GLYCERIN; PPG-9; ZINC SULFATE, UNSPECIFIED FORM; GUAR HYDROXYPROPYLTRIMONIUM CHLORIDE (1.7 SUBSTITUENTS PER SACCHARIDE); TRIETHANOLAMINE DODECYLBENZENESULFONATE; BUTYLENE GLYCOL; IODOPROPYNYL BUTYLCARBAMATE; METHYLCHLOROISOTHIAZOLINONE; METHYLISOTHIAZOLINONE

Dove Dermacare Scalp Dryness and Itch Relief Anti-Dandruff Shampoo

Active Ingredient

Pyrithione Zinc (1.0%)

Purpose

Anti-dandruff

Use

Helps prevent and control recurrence of itching, flaking and irritation associated with dandruff.

Warning

For external use only
When using this product Avoid contact with eyes. If contact occurs, rinse eyes thoroughly with water.
Stop use and ask a doctor if Condition worsens or does not improve after regular use of this product as directed.

KEEP OUT OF REACH OF CHILDREN

Keep this and all drugs out of reach of children. If swallowed, get medical help or contact a Poison Control Center right away.

Directions

For best results use at least twice per week or as directed by a doctor. Massage into scalp and hair. Rinse.

Inactive Ingredients

Water (Aqua), Sodium Laureth Sulfate, Cocamidopropyl Betaine, Sodium Chloride, Cocos Nucifera (Coconut) Oil, Butyrospermum Parkii (Shea) Butter, Carbomer, Fragrance (Parfum), Dimethiconol, DMDM Hydantoin, Citric Acid, Glycerin, PPG-9, Zinc Sulfate, Guar Hydroxypropyltrimonium Chloride, TEA-Dodecylbenzenesulfonate, Butylene Glycol, Iodopropynyl Butylcarbamate, Methylchloroisothiazolinone, Methylisothiazolinone

Questions, comments?

Call 1-800-761-3683

Gently cleanses & soothes itchy, dry scalp
For smooth, less frizzy hair
FLAKE FREE* + pH BALANCED
The solution that nourishes the scalp and relieves it from irritation

- Leaves hair flake free*
- Hydrates dry scalp
- Soothes itchy scalp
- Coconut & Shea butter indulgent scent
- For smooth, less frizzy hair

*No visible flakes with regular use